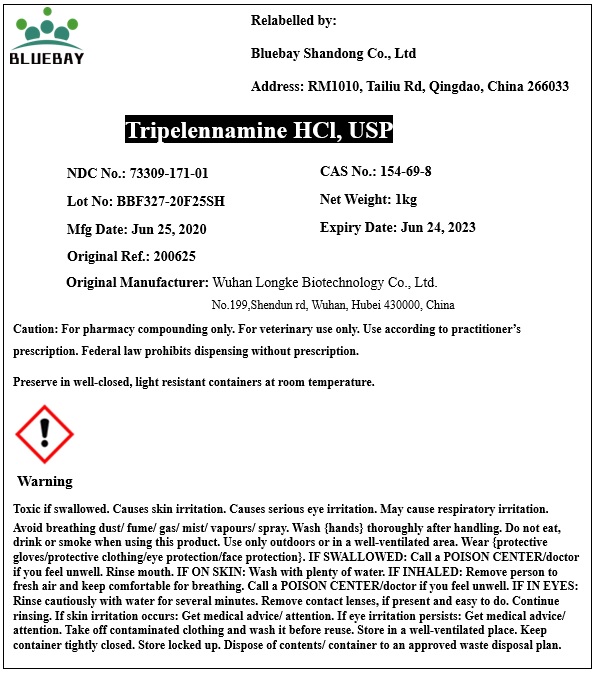 DRUG LABEL: Tripelennamine HCl
NDC: 73309-171 | Form: POWDER
Manufacturer: BLUEBAY SHANDONG CO.,LTD
Category: other | Type: BULK INGREDIENT
Date: 20200722

ACTIVE INGREDIENTS: TRIPELENNAMINE HYDROCHLORIDE 1 kg/1 kg

Tripelennamine HCl